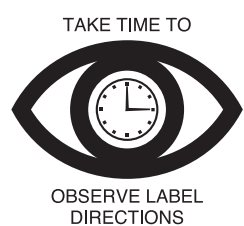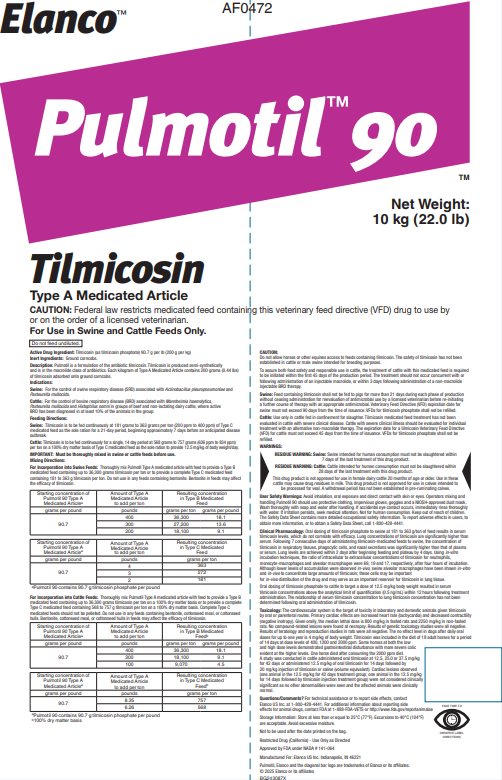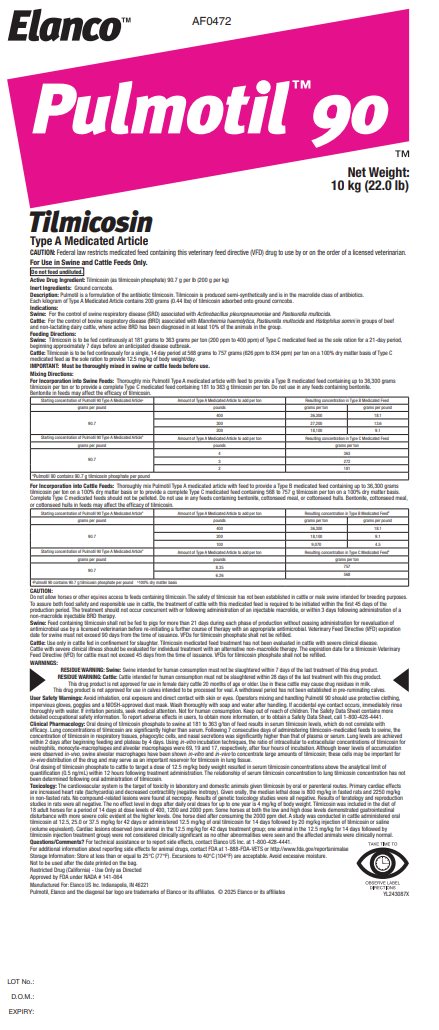 DRUG LABEL: Pulmotil 90
NDC: 58198-0472 | Form: GRANULE
Manufacturer: Elanco US Inc.
Category: animal | Type: VFD TYPE A MEDICATED ARTICLE ANIMAL DRUG LABEL
Date: 20251121

ACTIVE INGREDIENTS: tilmicosin phosphate 200 g/1 kg

Elanco™

AF0472

Pulmotil™ 90TM

Net Weight:

10 kg (22.0 lb)

Tilmicosin

Type A Medicated Article

CAUTION: Federal law restricts medicated feed containing this veterinary feed directive (VFD) drug to use by or on the order of a licensed veterinarian.

For Use in Swine and Cattle Feeds Only.

Do not feed undiluted.

Active Drug Ingredient: Tilmicosin (as tilmicosin phosphate) 90.7 g per lb (200 g per kg)

Inert Ingredients: Ground corncobs.

Description:

Pulmotil is a formulation of the antibiotic tilmicosin. Tilmicosin is produced semi-synthetically and is in the macrolide class of antibiotics. Each kilogram of Type A Medicated Article contains 200 grams (0.44 lbs) of tilmicosin adsorbed onto ground corncobs.

Indications:

Swine: For the control of swine respiratory disease (SRD) associated with Actinobacillus pleuropneumoniae and Pasteurella multocida.

Cattle: For the control of bovine respiratory disease (BRD) associated with Mannheimia haemolytica, Pasteurella multocida and Histophilus somni in groups of beef and non-lactating dairy cattle, where active BRD has been diagnosed in at least 10% of the animals in the group.

Feeding Directions:

Swine: Tilmicosin is to be fed continuously at 181 grams to 363 grams per ton (200 ppm to 400 ppm) of Type C medicated feed as the sole ration for a 21-day period, beginning approximately 7 days before an anticipated disease outbreak.

Cattle: Tilmicosin is to be fed continuously for a single, 14 day period at 568 grams to 757 grams (626 ppm to 834 ppm) per ton on a 100% dry matter basis of Type C medicated feed as the sole ration to provide 12.5 mg/kg of body weight/day.

IMPORTANT: Must be thoroughly mixed in swine or cattle feeds before use.

Mixing Directions:

For Incorporation into Swine Feeds: Thoroughly mix Pulmotil Type A medicated article with feed to provide a Type B medicated feed containing up to 36,300 grams tilmicosin per ton or to provide a complete Type C medicated feed containing 181 to 363 g tilmicosin per ton. Do not use in any feeds containing bentonite. Bentonite in feeds may affect the efficacy of tilmicosin.

Starting concentration of Pulmotil 90 Type A Medicated Articlea | Amount of Type A Medicated Article to add per ton | Resulting concentration in Type B Medicated Feed
grams per pound | pounds | grams per ton | grams per pound
90.7 | 400 | 36,300 | 18.1
90.7 | 300 | 27,200 | 13.6
90.7 | 200 | 18,100 | 9.1
Starting concentration of Pulmotil 90 Type A Medicated Articlea | Amount of Type A Medicated Article to add per ton | Resulting concentration in Type C Medicated Feed
grams per pound | pounds | grams per ton
90.7 | 4 | 363
90.7 | 3 | 272
90.7 | 2 | 181
aPulmotil 90 contains 90.7 g tilmicosin phosphate per pound

For Incorporation into Cattle Feeds: Thoroughly mix Pulmotil Type A medicated article with feed to provide a Type B medicated feed containing up to 36,300 grams tilmicosin per ton on a 100% dry matter basis or to provide a complete Type C medicated feed containing 568 to 757 g tilmicosin per ton on a 100% dry matter basis. Complete Type C medicated feeds should not be pelleted. Do not use in any feeds containing bentonite, cottonseed meal, or cottonseed hulls. Bentonite, cottonseed meal, or cottonseed hulls in feeds may affect the efficacy of tilmicosin.

Starting concentration of Pulmotil 90 Type A Medicated Articlea | Amount of Type A Medicated Article to add per ton | Resulting concentration in Type B Medicated Feedb
grams per pound | pounds | grams per ton | grams per pound
90.7 | 400 | 36,300 | 18.1
90.7 | 200 | 18,100 | 9.1
90.7 | 100 | 9,070 | 4.5
Starting concentration of Pulmotil 90 Type A Medicated Articlea | Amount of Type A Medicated Article to add per ton | Resulting concentration in Type C Medicated Feedb
grams per pound | pounds | grams per ton
90.7 | 8.35 | 757
90.7 | 6.26 | 568
aPulmotil 90 contains 90.7 g tilmicosin phosphate per pound
b100% dry matter basis

CAUTION:

Do not allow horses or other equines access to feeds containing tilmicosin. The safety of tilmicosin has not been established in cattle or male swine intended for breeding purposes.

To assure both food safety and responsible use in cattle, the treatment of cattle with this medicated feed is required to be initiated within the first 45 days of the production period. The treatment should not occur concurrent with or following administration of an injectable macrolide, or within 3 days following administration of a non-macrolide injectable BRD therapy.

Swine: Feed containing tilmicosin shall not be fed to pigs for more than 21 days during each phase of production without ceasing administration for reevaluation of antimicrobial use by a licensed veterinarian before re-initiating a further course of therapy with an appropriate antimicrobial. Veterinary Feed Directive (VFD) expiration date for swine must not exceed 90 days from the time of issuance. VFDs for tilmicosin phosphate shall not be refilled.

Cattle: Use only in cattle fed in confinement for slaughter. Tilmicosin medicated feed treatment has not been evaluated in cattle with severe clinical disease. Cattle with severe clinical illness should be evaluated for individual treatment with an alternative non-macrolide therapy. The expiration date for a tilmicosin Veterinary Feed Directive (VFD) for cattle must not exceed 45 days from the time of issuance. VFDs for tilmicosin phosphate shall not be refilled.

WARNINGS:

RESIDUE WARNING: Swine: Swine intended for human consumption must not be slaughtered within 7 days of the last treatment of this drug product.

RESIDUE WARNING: Cattle: Cattle intended for human consumption must not be slaughtered within 28 days of the last treatment with this drug product.

This drug product is not approved for use in female dairy cattle 20 months of age or older. Use in these cattle may cause drug residues in milk. This drug product is not approved for use in calves intended to be processed for veal. A withdrawal period has not been established in pre-ruminating calves.

User Safety Warnings: Avoid inhalation, oral exposure and direct contact with skin or eyes. Operators mixing and handling Pulmotil 90 should use protective clothing, impervious gloves, goggles and a NIOSH-approved dust mask. Wash thoroughly with soap and water after handling. If accidental eye contact occurs, immediately rinse thoroughly with water. If irritation persists, seek medical attention. Not for human consumption. Keep out of reach of children. The Safety Data Sheet contains more detailed occupational safety information. To report adverse effects in users, to obtain more information, or to obtain a Safety Data Sheet, call 1-800-428-4441.

CLINICAL PHARMACOLOGY

Clinical Pharmacology: Oral dosing of tilmicosin phosphate to swine at 181 to 363 g/ton of feed results in serum tilmicosin levels, which do not correlate with efficacy. Lung concentrations of tilmicosin are significantly higher than serum. Following 7 consecutive days of administering tilmicosin-medicated feeds to swine, the concentration of tilmicosin in respiratory tissues, phagocytic cells, and nasal secretions was significantly higher than that of plasma or serum. Lung levels are achieved within 2 days after beginning feeding and plateau by 4 days. Using in-vitro incubation techniques, the ratio of intracellular to extracellular concentrations of tilmicosin for neutrophils, monocyte-macrophages and alveolar macrophages were 69, 19 and 17, respectively, after four hours of incubation. Although lower levels of accumulation were observed in-vivo, swine alveolar macrophages have been shown in-vitro and in-vivo to concentrate large amounts of tilmicosin; these cells may be important for in-vivo distribution of the drug and may serve as an important reservoir for tilmicosin in lung tissue.

Oral dosing of tilmicosin phosphate to cattle to target a dose of 12.5 mg/kg body weight resulted in serum tilmicosin concentrations above the analytical limit of quantification (0.5 ng/mL) within 12 hours following treatment administration. The relationship of serum tilmicosin concentration to lung tilmicosin concentration has not been determined following oral administration of tilmicosin.

Toxicology: The cardiovascular system is the target of toxicity in laboratory and domestic animals given tilmicosin by oral or parenteral routes. Primary cardiac effects are increased heart rate (tachycardia) and decreased contractility (negative inotropy). Given orally, the median lethal dose is 800 mg/kg in fasted rats and 2250 mg/kg in non-fasted rats. No compound-related lesions were found at necropsy. Results of genetic toxicology studies were all negative. Results of teratology and reproduction studies in rats were all negative. The no effect level in dogs after daily oral doses for up to one year is 4 mg/kg of body weight. Tilmicosin was included in the diet of 18 adult horses for a period of 14 days at dose levels of 400, 1200 and 2000 ppm. Some horses at both the low and high dose levels demonstrated gastrointestinal disturbance with more severe colic evident at the higher levels. One horse died after consuming the 2000 ppm diet. A study was conducted in cattle administered oral tilmicosin at 12.5, 25.0 or 37.5 mg/kg for 42 days or administered 12.5 mg/kg of oral tilmicosin for 14 days followed by 20 mg/kg injection of tilmicosin or saline (volume equivalent). Cardiac lesions observed (one animal in the 12.5 mg/kg for 42 days treatment group; one animal in the 12.5 mg/kg for 14 days followed by tilmicosin injection treatment group) were not considered clinically significant as no other abnormalities were seen and the affected animals were clinically normal.

Questions/Comments? For technical assistance or to report side effects, contact Elanco US Inc. at 1-800-428-4441. For additional information about reporting side effects for animal drugs, contact FDA at 1-888-FDA-VETS or http://www.fda.gov/reportanimalae

Storage Information: Store at less than or equal to 25°C (77°F). Excursions to 40°C (104°F) are acceptable. Avoid excessive moisture.

Not to be used after the date printed on the bag.

Restricted Drug (California) - Use Only as Directed

Approved by FDA under NADA # 141-064

Manufactured For: Elanco US Inc. Indianapolis, IN 46221

Pulmotil, Elanco and the diagonal bar logo are trademarks of Elanco or its affiliates.

© 2025 Elanco or its affiliates

BG243087X
YL243087X

LOT No.:
D.O.M.:
EXPIRY:

Principal Display Panel – 22 lb Bag Label

Elanco™ AF0472

Pulmotil™ 90TM

Net Weight:
10 kg (22.0 lb)

Tilmicosin